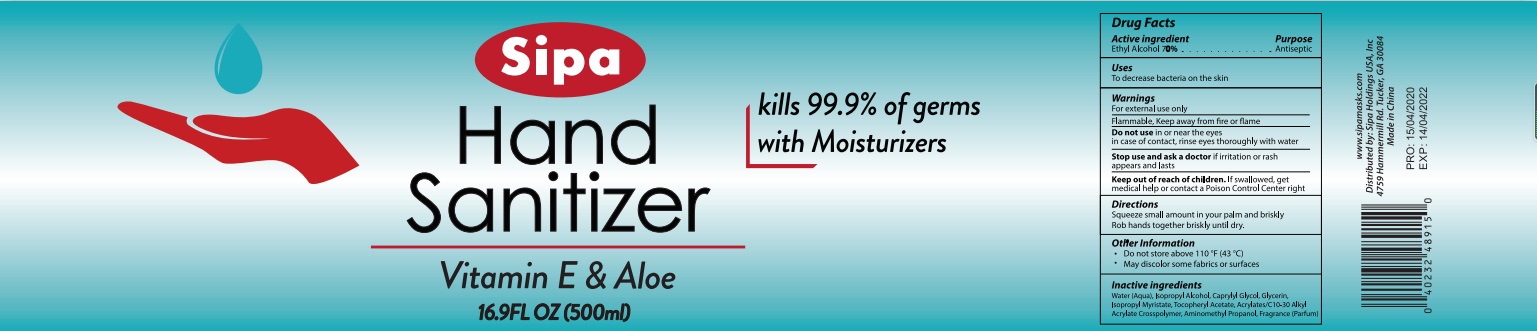 DRUG LABEL: Sipa Hand Sanitizer With Moisturizers Vitamin E and Aloe
NDC: 75780-018 | Form: GEL
Manufacturer: NINGBO MEINEKE Biotech Technology Co., Ltd.
Category: otc | Type: HUMAN OTC DRUG LABEL
Date: 20200601

ACTIVE INGREDIENTS: alcohol 70 mL/100 mL
INACTIVE INGREDIENTS: WATER; PROPYLENE GLYCOL; ALOE VERA LEAF; ISOPROPYL ALCOHOL; CAPRYLYL GLYCOL; GLYCERIN; ISOPROPYL MYRISTATE; .ALPHA.-TOCOPHEROL ACETATE, D-; CARBOMER COPOLYMER TYPE A; AMINOMETHYLPROPANOL

Drug facts

Active ingredient - Ethyl Alcohol 71%

Purpose - Antiseptic

KEEP OUT OF REACH OF CHILDREN

If swallowed, get medical help or contact a Poison Control Center right away

INDICATIONS AND USAGE

To decrease bacteria on the skin

WARNINGS

For external use only.
Flammable. Keep away from fire or flame.

Do not use in or near the eyes, in case of contact, rinse eyes thoroughly with water

Stop using and ask a doctor, if irritation or rash appears and lasts.

Other information:

Store below 110℉（43℃）

May discolor certain fabrics or surfaces.

DOSAGE AND ADMINISTRATION

Squeeze small amount in your palm and briskly

Rob hands together briskly until dry

INACTIVE INGREDIENT

Water （Aqua）, Isopropyl Alcohol, Caprylyl Glycol, Glycerin, Isopropyl Myristate, Tocopheryl Acetate, AcrylatesC-10-30 Alkyl Acrylate Crosspolymer, Aminomethyl Propanol, Fragrance (Parfum)